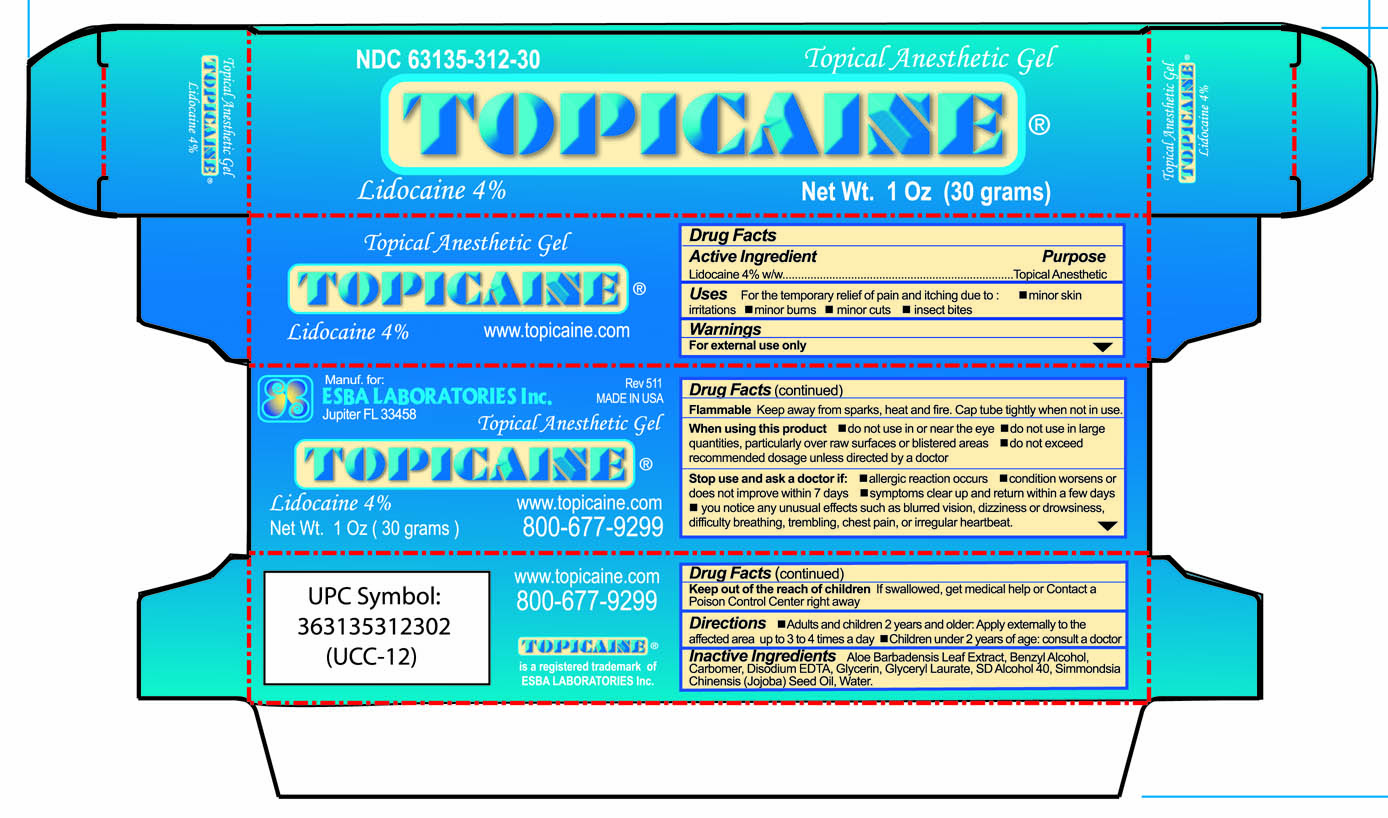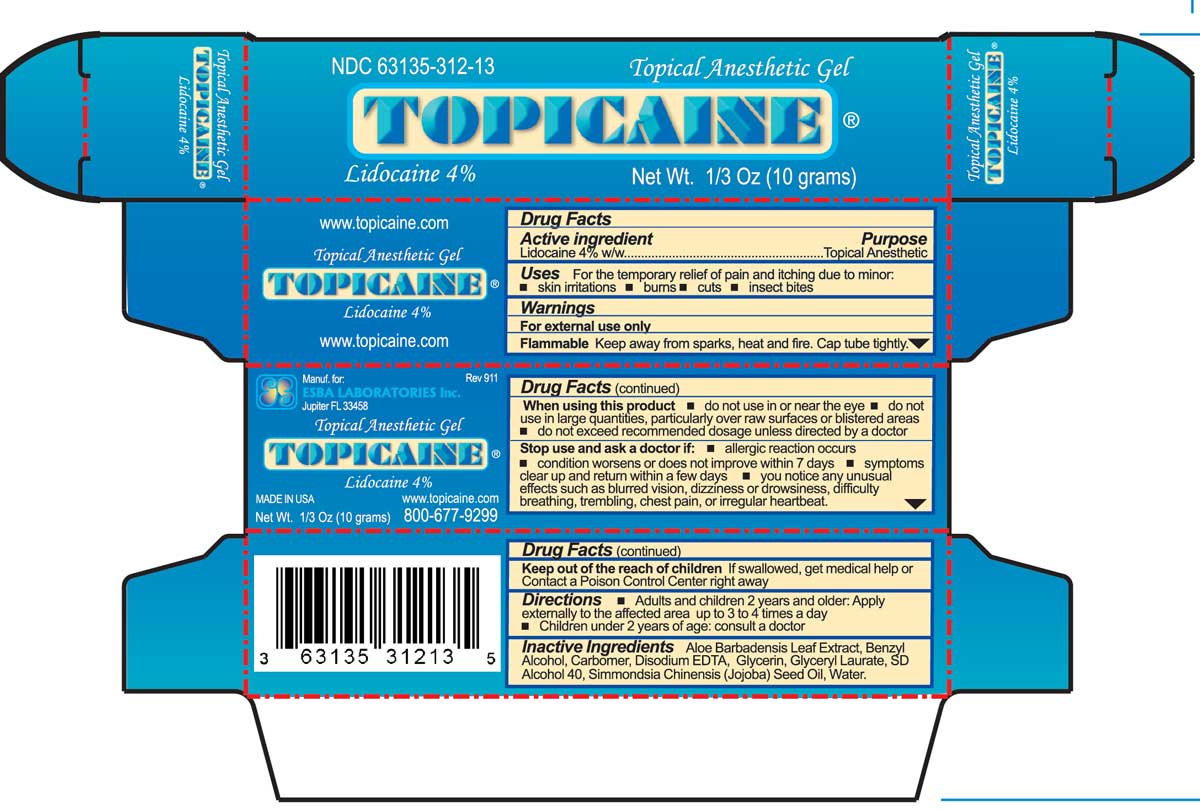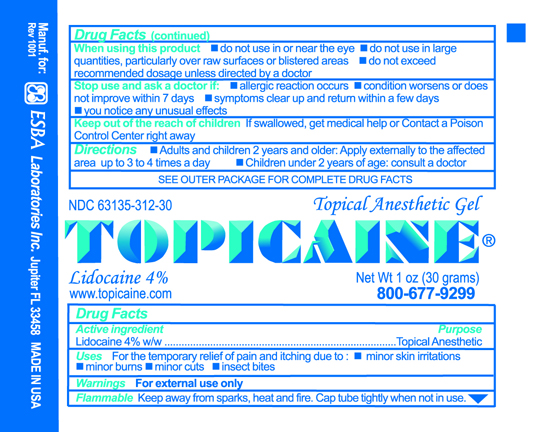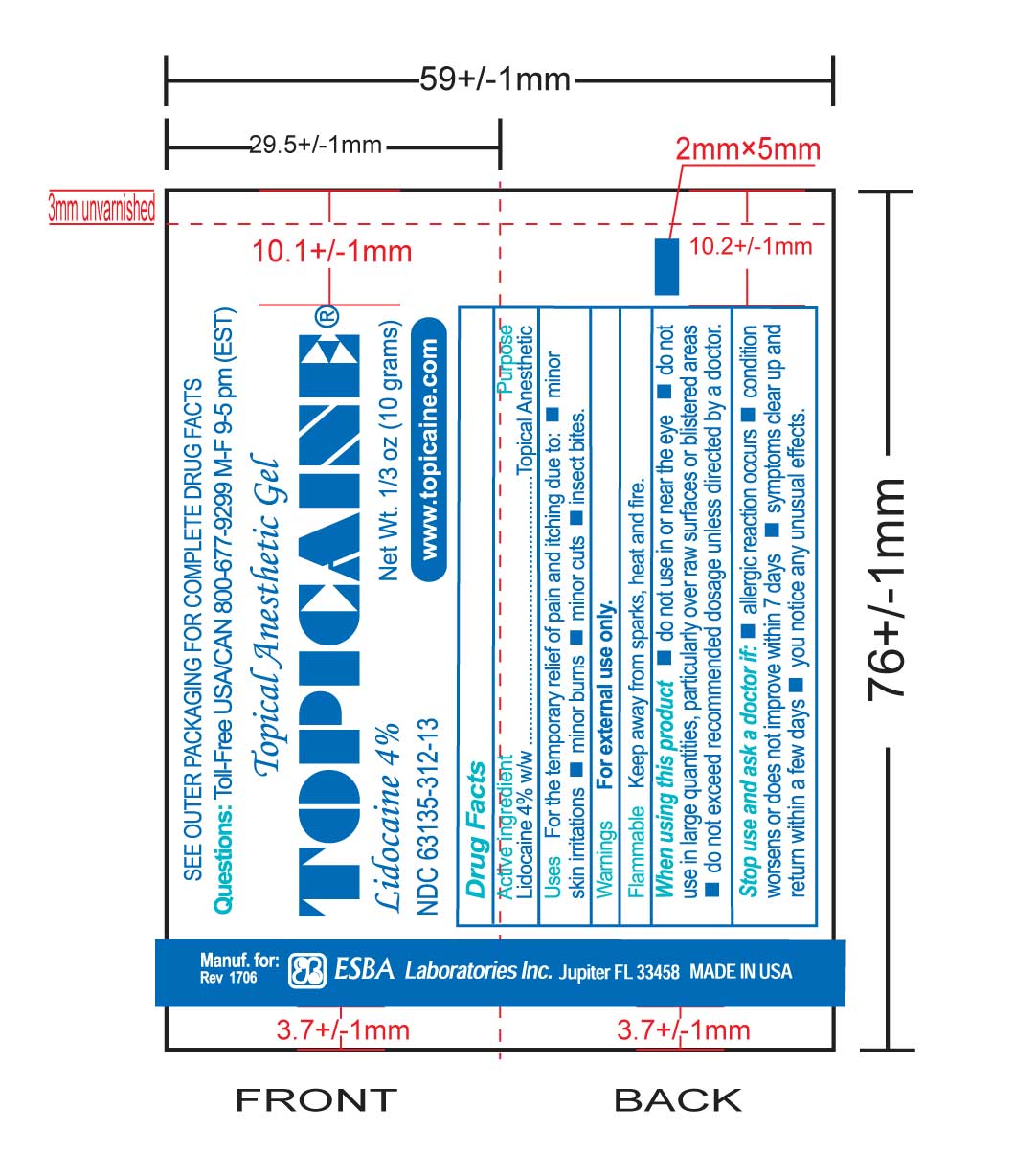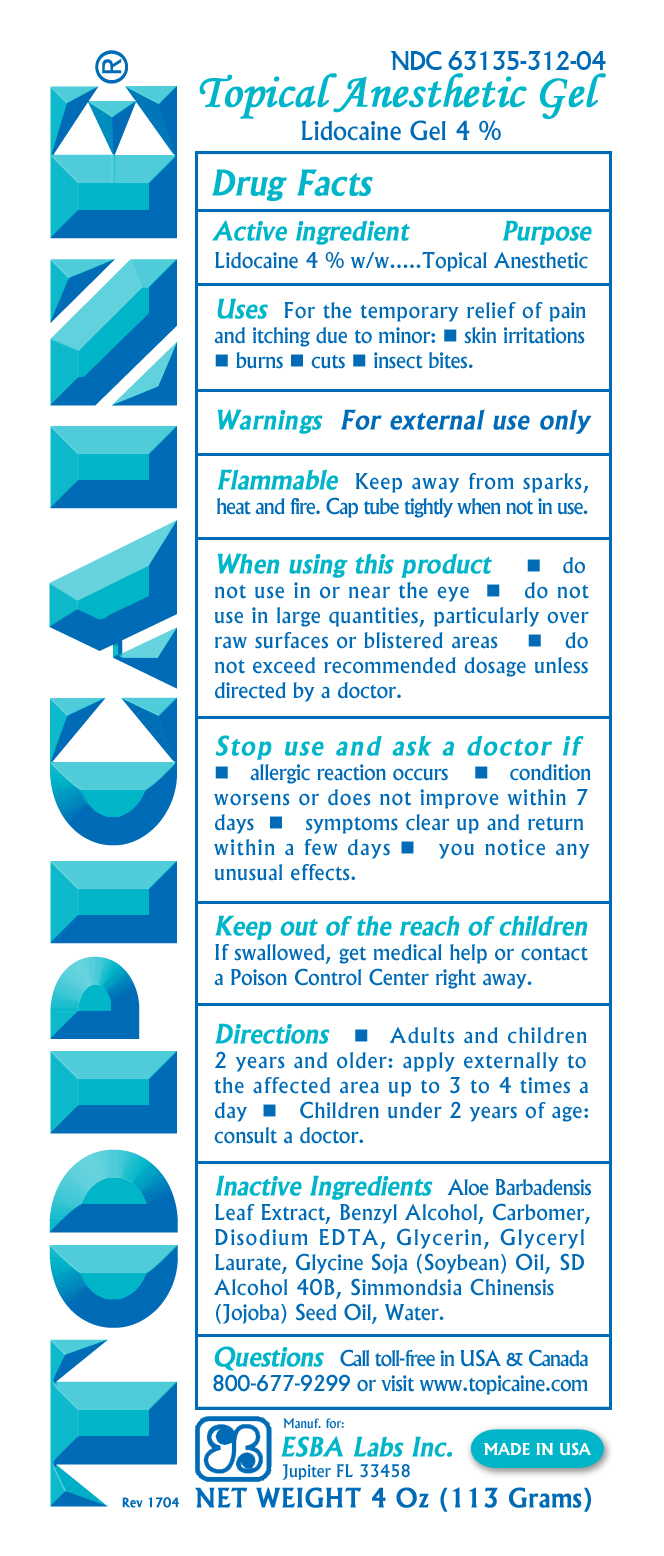 DRUG LABEL: TOPICAINE
NDC: 63135-312 | Form: GEL
Manufacturer: ESBA LABORATORIES INC.
Category: otc | Type: HUMAN OTC DRUG LABEL
Date: 20240919

ACTIVE INGREDIENTS: LIDOCAINE 4 g/100 g
INACTIVE INGREDIENTS: WATER 44.534 g/100 g; CARBOMER 940 0.6 g/100 g; ALCOHOL 36.842 g/100 g; JOJOBA OIL 2.5 g/100 g; GLYCERYL LAURATE 2 g/100 g; ALOE VERA LEAF 2.5 g/100 g; BENZYL ALCOHOL 2 g/100 g; GLYCERIN 5 g/100 g; EDETATE DISODIUM 0.024 g/100 g

TOPICAINE

Active ingredient

Lidocaine 4% w/w

Purpose

Topical Anesthetic

Uses

For the temporary relief of pain.

Warnings

For external use only

Flammable

Keep away from sparks, heat and fire. Cap tube tightly when not in use.

Stop use and ask a doctor if:

- allergic reaction occurs
- condition worsens or does not improve within 7 days
- symptoms clear up and return within a few days
- you notice any unusual effects

Keep out of the reach of children

If swallowed, get medical help or contact a Poison Control Center right away.

Directions

Apply externally to affected area up to 3 to 4 times a day. Children under 2 years of age consult a doctor.

Inactive Ingredients

Aloe Barbadensis Leaf Extract, Benzyl Alcohol, Carbomer, Disodium EDTA, Glycerin, Glyceryl Laurate, SD Alcohol 40B, Simmondsia Chinensis (Jojoba) Seed Oil, Water

Questions

Call toll-free in USA & Canada 800-677-9299 or visit www.topicaine.com

Labelling on tubes and outer cartons

Labelling printed on tube of Topicaine 4% 10 gram tube:

Outer carton of Topicaine 4% 10 grams:

Label affixed to Topicaine 4% 30 gram tubes:

Outer box of Topicaine 4% 30 grams:

Label affixed to tubes of Topicaine 4% 113 grams: